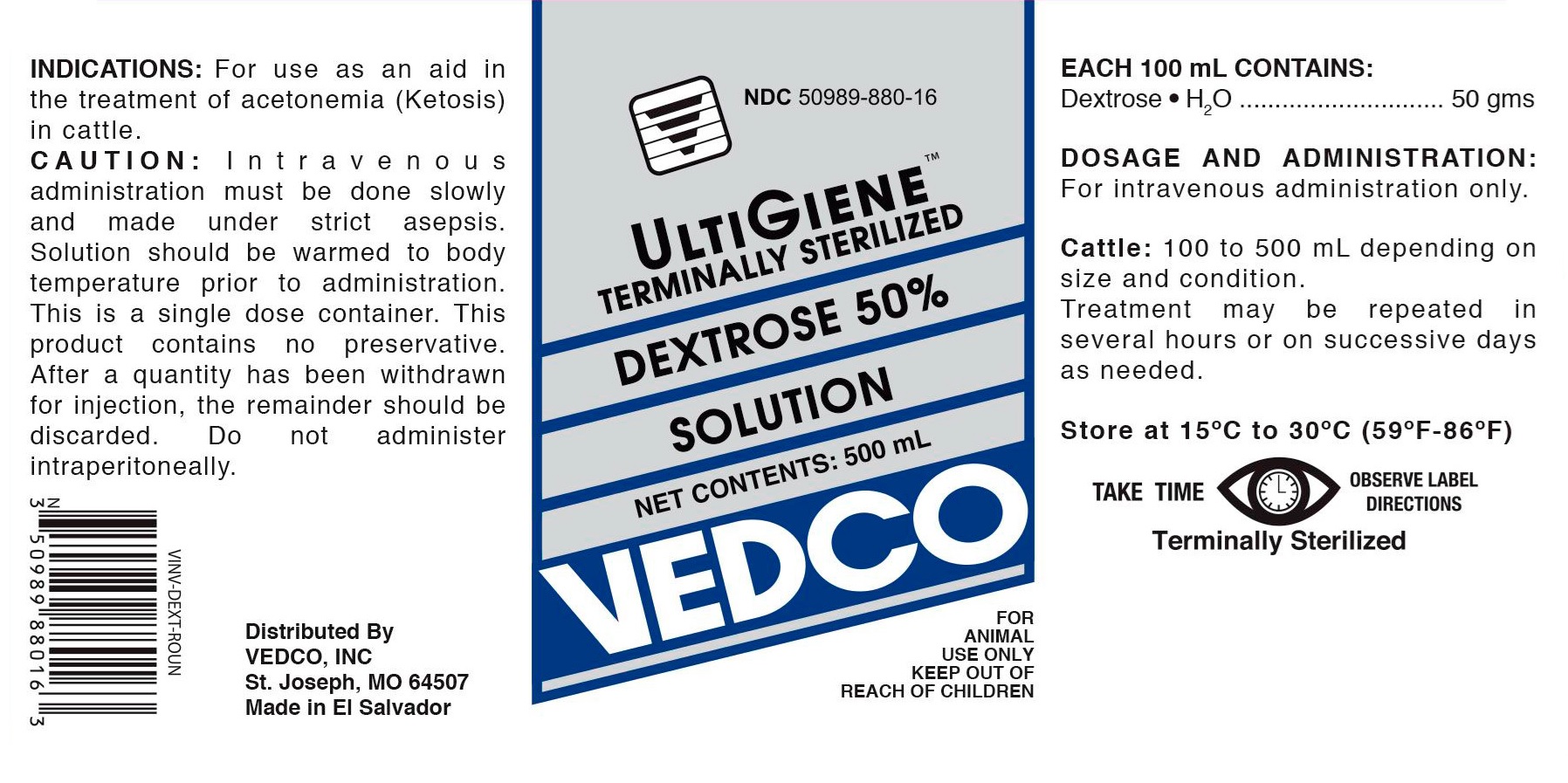 DRUG LABEL: Dextrose
NDC: 50989-880 | Form: INJECTION, SOLUTION
Manufacturer: Vedco
Category: animal | Type: OTC ANIMAL DRUG LABEL
Date: 20190501

ACTIVE INGREDIENTS: DEXTROSE MONOHYDRATE 50 g/100 mL

DEXTROSE 50% SOLUTION

DEXTROSE- dextrose injection, solution

Vedco

Disclaimer: This drug has not been found by FDA to be safe and effective, and this labeling has not been approved by FDA.

DEXTROSE 50% SOLUTION

KEEP OUT OF REACH OF CHILDREN

ACTIVE INGREDIENTS:

Each 100 mL contains:

Dextrose . H2 O .......................... 50 gms.

DOSAGE AND ADMINISTRATION:

For intravenous administration only.

Cattle: 100 to 500 mL depending on size and condition.

Treatment may be repeated in several hours or on successive days as needed.

STORAGE

Store at 15 degrees C to 30 degrees C (59 degrees F-86 degrees F).

INDICATIONS:

For use as an aid in the treatment of acetonemia (Ketosis) in cattle.

CAUTION:

Intravenous administration must be done slowly and made under strict asepsis. Solution should be warmed to body temperature prior to administration.

This is a single dose container. This product contains no preservative. After a quantity has been withdrawn for injection, the remainder should be discarded. Do not administer intraperitoneally.

VETERINARY INDICATIONS

FOR ANIMAL USE ONLY

SAFE HANDLING WARNING

TAKE TIME OBSERVE LABEL DIRECTIONS

INFORMATION FOR OWNERS/CAREGIVERS

Distributed By
VEDCO, INC.
St. Joseph, MO 64507

Made in El Salvador

TABLE
CONTENTS | NDC | VINV #
500 mL | 50989-880-16 | VINV-DEXT-ROUN

PRINCIPAL DISPLAY PANEL

NDC 50989-880-16

ULTIGIENE TERMINALLY STERILIZED

DEXTROSE 50% SOLUTIONS

NET CONTENTS: 500 mL

VEDCO

FOR ANIMAL USE ONLY

KEEP OUT OF REACH OF CHILDREN